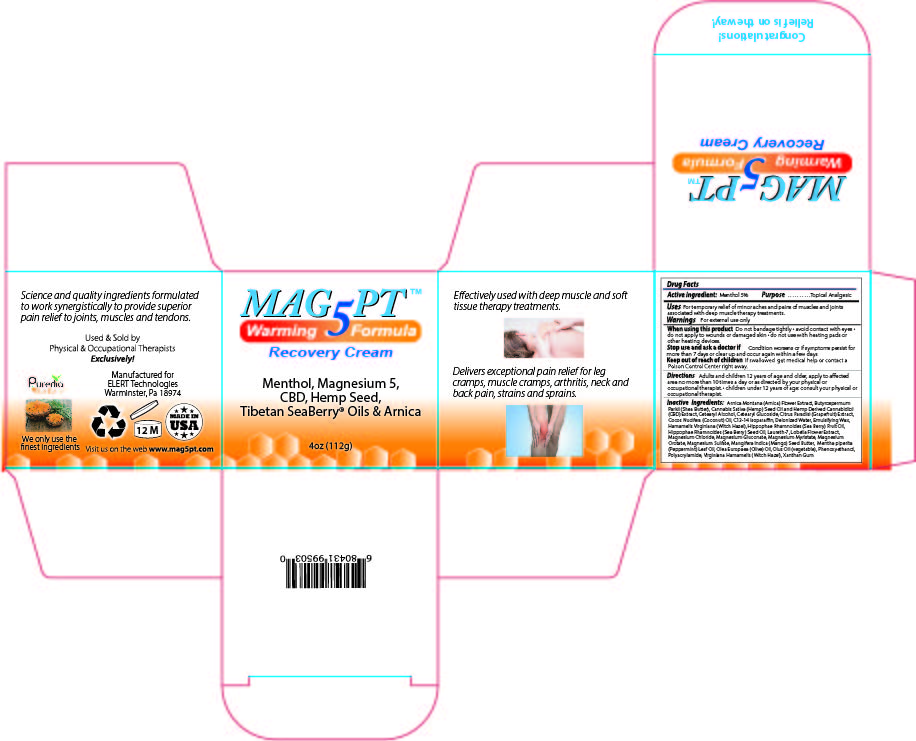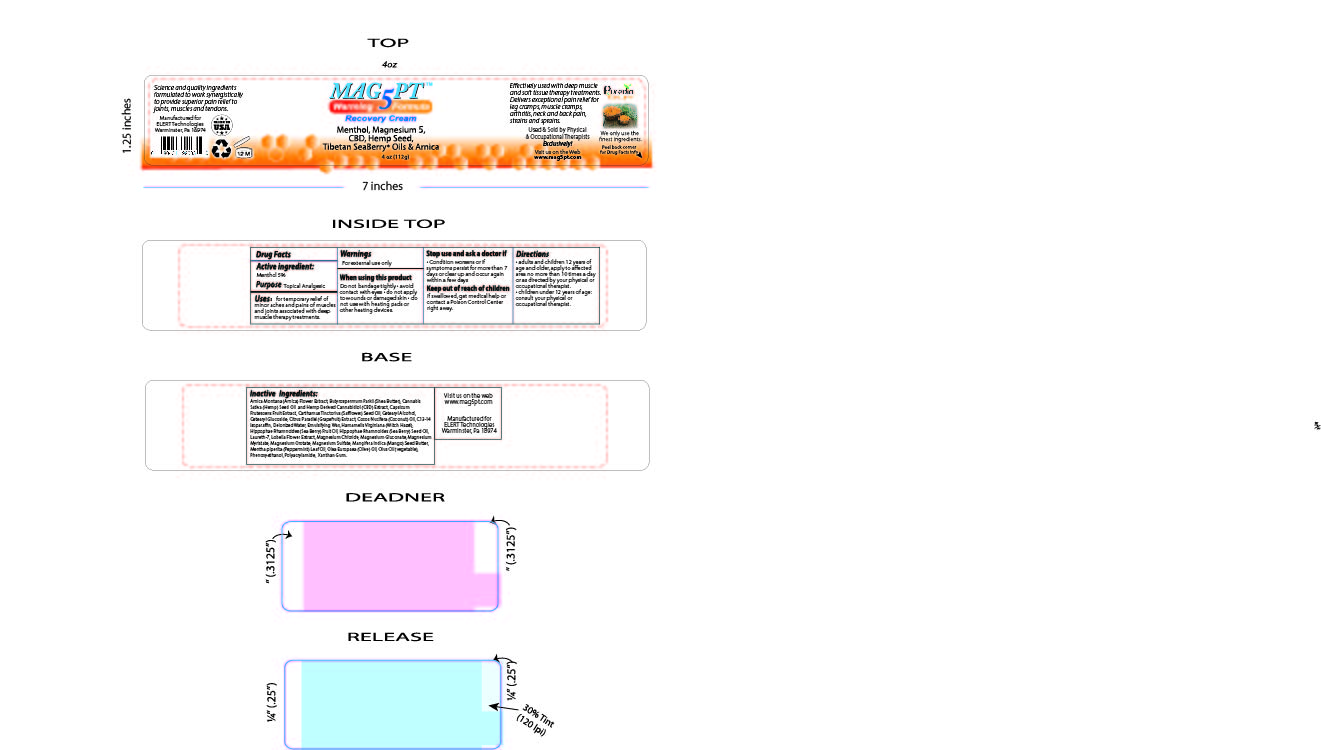 DRUG LABEL: MAG 5 PT WARMING FORMULA
NDC: 76348-511 | Form: CREAM
Manufacturer: RENU LABORATORIES, LLC
Category: otc | Type: HUMAN OTC DRUG LABEL
Date: 20251118

ACTIVE INGREDIENTS: MENTHOL 5.6 g/112 g
INACTIVE INGREDIENTS: WATER; GLYCERYL MONOSTEARATE; OLIVE OIL; PEG-100 STEARATE; WITCH HAZEL; SHEA BUTTER; LAURETH-7; PEPPERMINT OIL; HIPPOPHAE RHAMNOIDES SEED OIL; C13-14 ISOPARAFFIN; WHITE WAX; ARNICA MONTANA FLOWER; LOBELIA INFLATA LEAF; STEARIC ACID; COCONUT OIL; MAGNESIUM MYRISTATE; TABASCO PEPPER; MANGIFERA INDICA SEED BUTTER; NIACINAMIDE; CANNABIS SATIVA SEED OIL; CORN OIL; MAGNESIUM OROTATE; CANNABIDIOL; MAGNESIUM GLUCONATE; HIPPOPHAE RHAMNOIDES FRUIT OIL; CETEARYL GLUCOSIDE; PHENOXYETHANOL; MAGNESIUM SULFATE, UNSPECIFIED; POLYACRYLAMIDE (10000 MW); MAGNESIUM CHLORIDE; CETOSTEARYL ALCOHOL

MAG 5 PT WARMING FORMULA RECOVERY CREAM

ACTIVE INGREDIENT

Menthol 5%

PURPOSE

Topical Analgesic

INDICATIONS AND USAGE

For temporary relief of minor aches and pains of muscles and joints associated with deep muscle therapy treatments.

WARNINGS

For external use only

WHEN USING

Do not bandage tightly

- avoid contact with eyes
- do not apply to wounds or damaged skin
- do not use with heating pads or other heating devices.

Stop use and ask a doctor if

- Condition worsens or if symptoms persist for more than 7 days or clear up and occur again within a few days

KEEP OUT OF REACH OF CHILDREN

If swallowed, get medical help or contact a Poison Control Center right away.

Directions

- adults and children 12 years of age and older, apply to affected area no more than 10 times a day or as directed by your physical or occupational therapist
- children under 12 years of age, do not use, consult a doctor.

INACTIVE INGREDIENT

Arnica Montana (Arnica) Flower Extract, Butyrospermum Parkii (Shea) Butter, Cannabis Sativa (Hemp) Seed Oil, Cetearyl Alcohol, Cetearyl Glucoside, Cocos Nucifera (Coconut) Oil, Deionized Water, Emulsifying Wax, Fragrance, Hamamelis Virginiana (Witch Hazel), Hemp Derived Cannabidiol (CBD) Extract, Laureth-7, Lobelia Inflata (Lobelia) Extract, Magnesium Chloride, Magnesium Citrate, Magnesium Gluconate, Magnesium Myristate, Magnesium Sulfate, Mangifera Indica (Mango) Seed Buter, Mentha Piperita (Peppermint) Oil, Olea Europaea (Olive) Oil, Olus Oil (Vegetable), Phenoxyethanol, Polyacrylamide C13-14 Isoparaffin, Xanthan Gum

MAG5 PT WARMING CREAM LABEL AND PRODUCT BOX